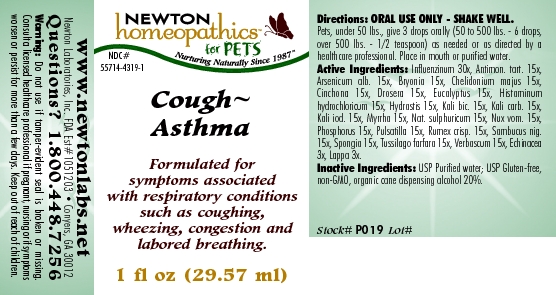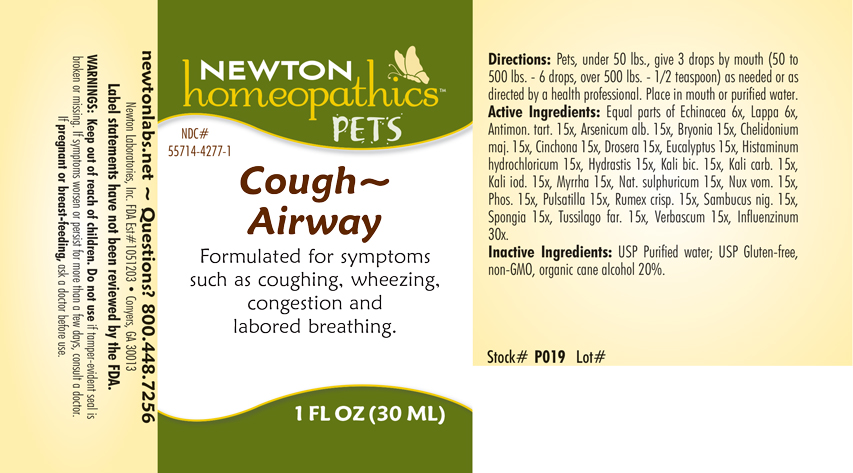 DRUG LABEL: Cough - Asthma
NDC: 55714-4319 | Form: LIQUID
Manufacturer: Newton Laboratories, Inc.
Category: homeopathic | Type: OTC ANIMAL DRUG LABEL
Date: 20190114

ACTIVE INGREDIENTS: Influenza A Virus 30 [hp_X]/1 mL; Antimony Potassium Tartrate 15 [hp_X]/1 mL; Arsenic Trioxide 15 [hp_X]/1 mL; Bryonia Alba Root 15 [hp_X]/1 mL; Chelidonium Majus 15 [hp_X]/1 mL; Cinchona Officinalis Bark 15 [hp_X]/1 mL; Drosera Rotundifolia Flowering Top 15 [hp_X]/1 mL; Eucalyptus Globulus Leaf 15 [hp_X]/1 mL; Histamine Dihydrochloride 15 [hp_X]/1 mL; Goldenseal 15 [hp_X]/1 mL; Potassium Dichromate 15 [hp_X]/1 mL; Potassium Carbonate 15 [hp_X]/1 mL; Potassium Iodide 15 [hp_X]/1 mL; Myrrh 15 [hp_X]/1 mL; Sodium Sulfate 15 [hp_X]/1 mL; Strychnos Nux-vomica Seed 15 [hp_X]/1 mL; Phosphorus 15 [hp_X]/1 mL; Pulsatilla Vulgaris 15 [hp_X]/1 mL; Rumex Crispus Root 15 [hp_X]/1 mL; Sambucus Nigra Flowering Top 15 [hp_X]/1 mL; Spongia Officinalis Skeleton, Roasted 15 [hp_X]/1 mL; Tussilago Farfara 15 [hp_X]/1 mL; Verbascum Thapsus 15 [hp_X]/1 mL; Echinacea, Unspecified 3 [hp_X]/1 mL; Arctium Lappa Root 3 [hp_X]/1 mL; Influenza B Virus 30 [hp_X]/1 mL
INACTIVE INGREDIENTS: Alcohol; Water

Cough - Asthma

INDICATIONS & USAGE SECTION

Cough - Airway Formulated for symptoms such as coughing, wheezing, congestion and labored breathing.

DOSAGE & ADMINISTRATION SECTION

Directions: Pets, under 50 lbs., give 3 drops by mouth (50 to 500 lbs. - 6 drops, over 500 lbs. - 1/2 teaspoon) as needed or as directed by a health professional. Place in mouth or purified water.

OTC - ACTIVE INGREDIENT SECTION

Equal parts of Echinacea 3x, Lappa 3x, Antimon. tart. 15x, Arsenicum alb. 15x, Bryonia 15x, Chelidonium majus 15x, Cinchona 15x, Drosera 15x, Eucalyptus 15x, Histaminum hydrochloricum 15x, Hydrastis 15x, Kali bic. 15x, Kali carb. 15x, Kali iod. 15x, Myrrha 15x, Nat. sulphuricum 15x, Nux vom. 15x, Phosphorus 15x, Pulsatilla 15x, Rumex crisp. 15x, Sambucus nig.15x, Spongia 15x, Tussilago farfara 15x, Verbascum 15x, Influenzinum 30x.

OTC - PURPOSE SECTION

Formulated for symptoms such as coughing, wheezing, congestion and labored breathing.

INACTIVE INGREDIENT SECTION

Inactive Ingredients: USP Purified Water; USP Gluten-free, non-GMO, organic cane alcohol 20%.

QUESTIONS SECTION

newtonlabs.net Questions? 1.800.448.7256 Newton Laboratories, Inc. FDA Est # 1051203 - Conyers, GA 30013
Label statements have not been reviewed by the FDA.

WARNINGS SECTION

Warnings: Keep out of reach of children. Do not use if tamper-seal is broken or missing. If symptoms worsen or persist for more than a few days, consult a doctor.

OTC - PREGNANCY OR BREAST FEEDING SECTION

If pregnant or breast-feeding, ask a doctor before use.

OTC - KEEP OUT OF REACH OF CHILDREN SECTION

Keep out of reach of children.